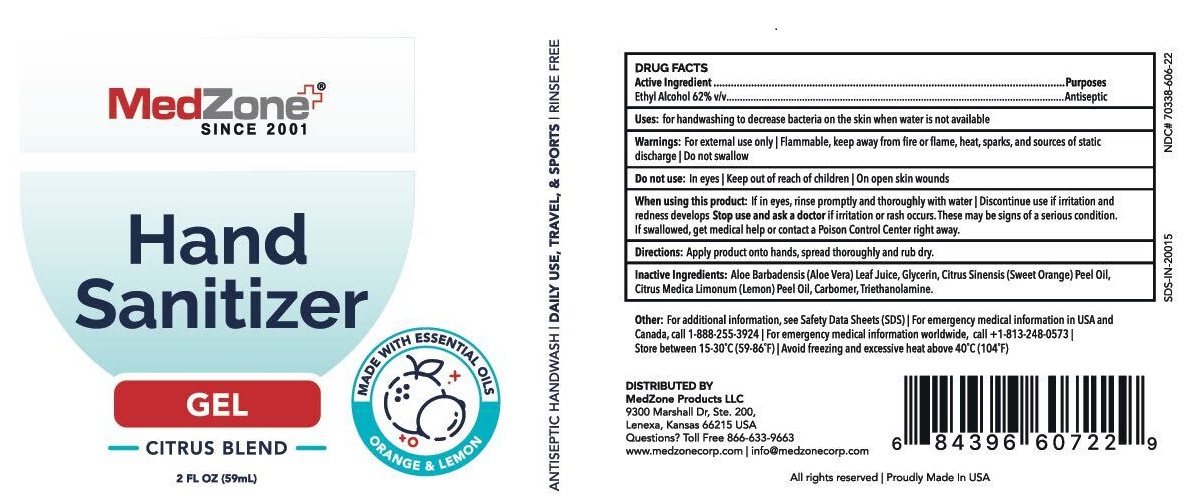 DRUG LABEL: Hand Sanitizer Citrus Blend
NDC: 70338-606 | Form: GEL
Manufacturer: MedZone Products, LLC
Category: otc | Type: HUMAN OTC DRUG LABEL
Date: 20200617

ACTIVE INGREDIENTS: ALCOHOL 0.62 mL/1 mL
INACTIVE INGREDIENTS: CARBOMER HOMOPOLYMER, UNSPECIFIED TYPE; ALOE VERA LEAF; GLYCERIN; TROLAMINE; ORANGE OIL; LEMON OIL

Hand Sanitizer Citrus Blend

DRUG FACTS

Active Ingredient

Ethyl Alcohol 62% v/v

Purposes

Antiseptic

Uses:

for handwashing to decrease bacteria on the skin when water is not available

Warnings:

For external use only | Flammable, keep away from fire or flame, heat, sparks, and sources of static discharge | Do not swallow

Do not use:

In eyes | Keep out of reach of children | On open skin wounds

When using this product:

If in eyes, rinse promptly and thoroughly with water | Discontinue use if irritation and redness develops

Stop use and ask a doctor

If irritation or rash occurs. These may be signs of a serious condition. If swallowed, get medical help or contact a Poison Control Center right away.

Directions:

Apply product onto hands, spread thoroughly and rub dry.

Inactive Ingredients:

Aloe Barbadensis (Aloe Vera) Leaf Juice, Glycerin, Citrus Sinensis (Sweet Orange) Peel Oil, Citrus Medica Limonum (Lemon) Peel Oil, Carbomer, Triethanolamine.

Other:

For additional information, see Safety Data Sheets (SDS) | For emergency medical information in USA and Canada, call 1-888-255-3924 | For emergency medical information worldwide, call 1-813-248-0573 | Store between 15-30°C (59-86°F) | Avoid freezing and excessive heat above 40°C (104°F)

DISTRIBUTED BY
MedZone Products LLC
9300 Marshall Dr, Ste. 200,
Lenexa, Kansas 66215 USA

Questions?

Toll Free 866-633-9663

www.medzonecorp.com | info@medzonecorp.com

PRINCIPAL DISPLAY PANEL - 59 mL Bottle Label

MedZone ®

SINCE 2001

Hand Sanitizer

GEL

-CITRUS BLEND-

2 FL OZ (59mL)